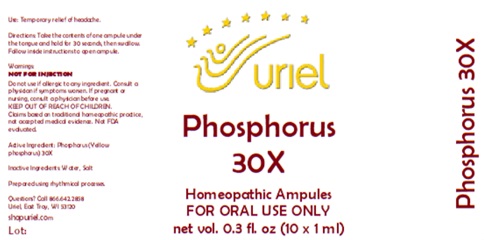 DRUG LABEL: Phosphorus 30
NDC: 48951-8023 | Form: LIQUID
Manufacturer: Uriel Pharmacy Inc.
Category: homeopathic | Type: HUMAN OTC DRUG LABEL
Date: 20260225

ACTIVE INGREDIENTS: PHOSPHORUS 30 [hp_X]/1 mL
INACTIVE INGREDIENTS: SODIUM CHLORIDE; WATER

Phosphorus 30

PURPOSE

Use: Temporary relief of headache.

INDICATIONS AND USAGE

FOR ORAL USE ONLY

DOSAGE AND ADMINISTRATION

Directions: Take the contents of one ampule under the tongue and hold for 30 seconds, then swallow. Follow inside instructions to open ampule.

Warnings:
NOT FOR INJECTION
Do not use if allergic to any ingredient. Consult a physician if symptoms worsen. If pregnant or nursing, consult a physician before use.
Claims based on traditional homeopathic practice, not accepted medical evidence. Not FDA evaluated.

KEEP OUT OF REACH OF CHILDREN.

Active Ingredient: Phosphorus (Yellow phosphorus) 30X

Inactive Ingredients: Water, Salt

Prepared using rhythmical processes.

QUESTIONS

Questions? Call 866.642.2858 Uriel, East Troy, WI 53120 shopuriel.com

Lot: